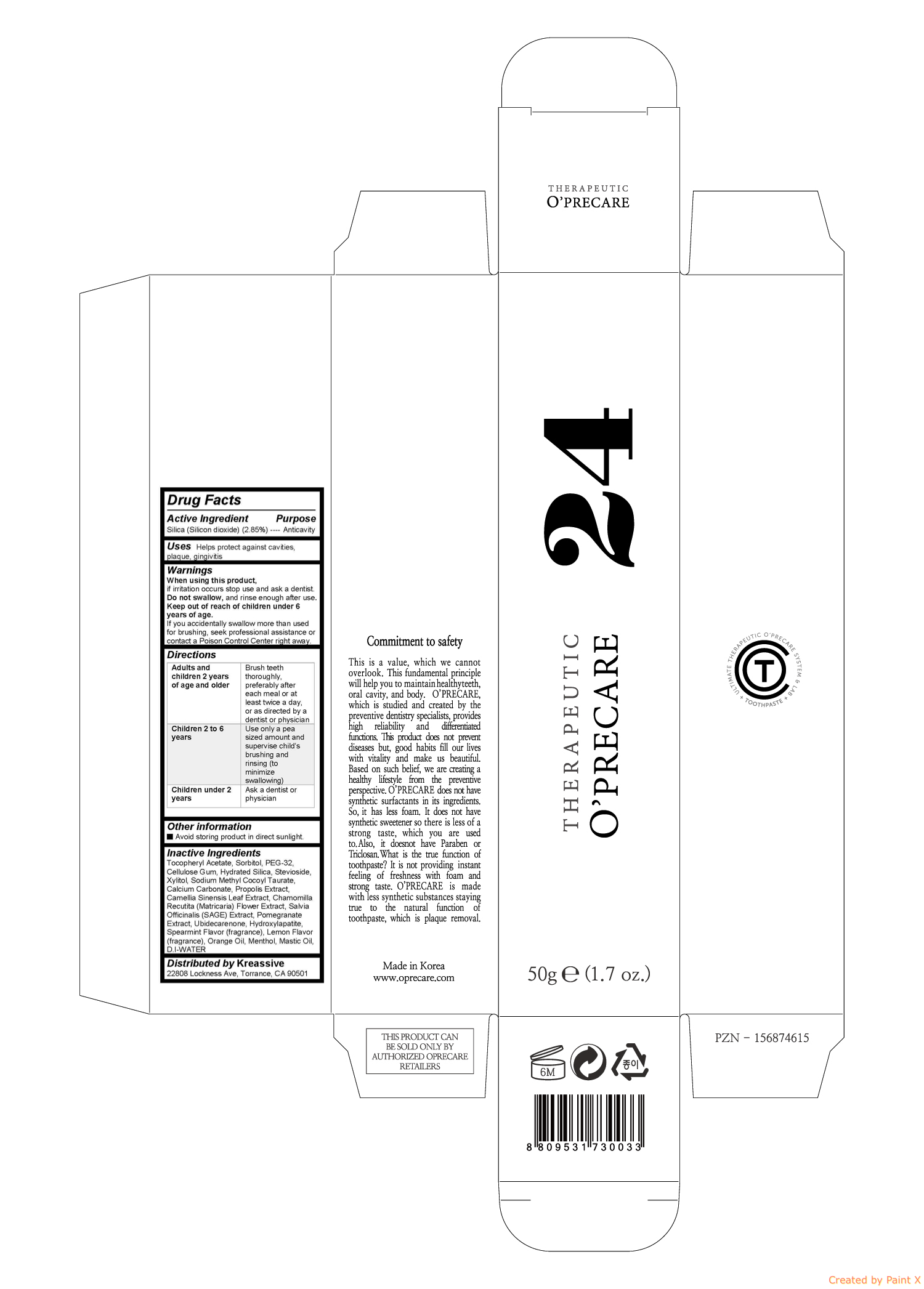 DRUG LABEL: OPRECARE 24
NDC: 71764-103 | Form: GEL
Manufacturer: O'PRECARE
Category: otc | Type: HUMAN OTC DRUG LABEL
Date: 20171012

ACTIVE INGREDIENTS: SILICON DIOXIDE 1.425 g/50 g
INACTIVE INGREDIENTS: .ALPHA.-TOCOPHEROL ACETATE; SORBITOL; POLYETHYLENE GLYCOL 1500; CARBOXYMETHYLCELLULOSE SODIUM, UNSPECIFIED FORM; HYDRATED SILICA; STEVIOSIDE; Xylitol; SODIUM METHYL COCOYL TAURATE; Calcium Carbonate; PROPOLIS WAX; GREEN TEA LEAF; CHAMOMILE; SALVIA OFFICINALIS ROOT; POMEGRANATE; Ubidecarenone; TRIBASIC CALCIUM PHOSPHATE; ORANGE OIL; Menthol

O'PRECARE 24

Active ingredient

Silica (Silicon dioxide) (2.85%)

Purpose

Anticavity

Warnings

When using this product, if irritation occurs stop use and ask a dentist. Do not swallow, and rinse enough after use. Keep out of reach of children under 6 years of age. If you accidentally swallow more than used for brushing, seek professional assistance or contact a Poison Control Center right away.

Uses

Helps protect against cavities, plaque, gingivitis

Directions

Adults and children 2 years of age and older | Brush teeth thoroughly, preferably after each meal or at least twice a day, or as directed by a dentist or physician
Children 2 to 6 years | Use only a pea sized amount and supervise childs brushing and rinsing (to minimize swallowing)
Children under 2 years | Ask a dentist or physician

Keep out of reach of children under 6 years of age. If you accidentally swallow more than used for brushing, seek professional assistance or contact a Poison Control Center right away.

Inactive ingredients

Silica, Tocopheryl Acetate, Sorbitol, PEG-32, Xylitol, Stevioside, Hydrated Silica, Cellulose Gum, Sodium Methyl Cocoyl Taurate, Menthol, Liquorice, Propolis Extract, Allantoin, Piridokssin Hydrochloride, Camellia Sinensis Leaf Extract, Citron Flavor (fragrance), Lemon Oil, Orange Oil, Eucalyptus Oil, D.I-WATER